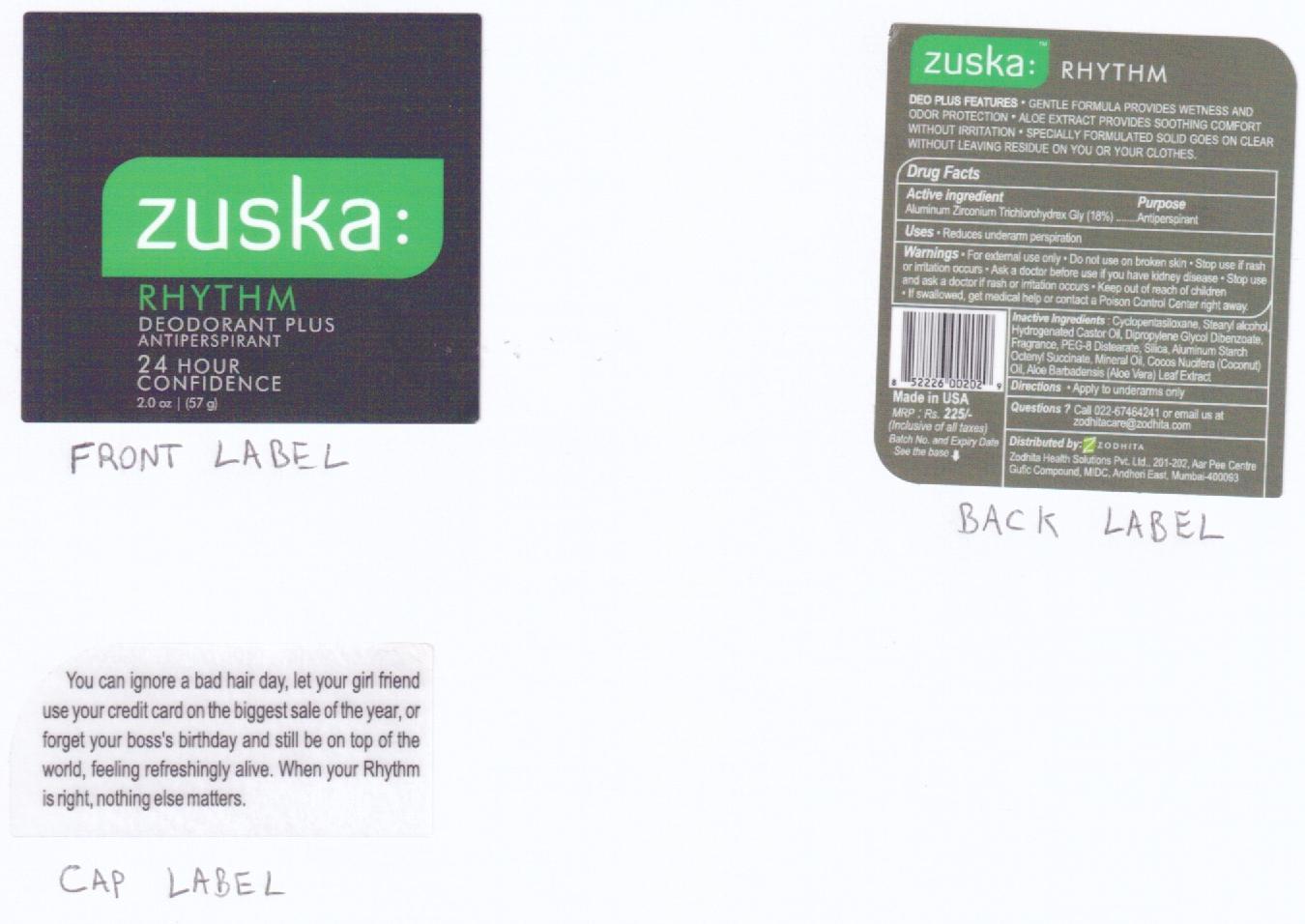 DRUG LABEL: ZUSKA
NDC: 53135-838 | Form: STICK
Manufacturer: RAANI CORPORATION
Category: otc | Type: HUMAN OTC DRUG LABEL
Date: 20130424

ACTIVE INGREDIENTS: ALUMINUM ZIRCONIUM TRICHLOROHYDREX GLY 180 mg/1 g
INACTIVE INGREDIENTS: CYCLOMETHICONE 5; STEARYL ALCOHOL; HYDROGENATED CASTOR OIL; DIPROPYLENE GLYCOL DIBENZOATE; PEG-8 DISTEARATE; SILICON DIOXIDE; ALUMINUM STARCH OCTENYLSUCCINATE; MINERAL OIL; COCONUT OIL; ALOE VERA LEAF

Drug Facts

Active Ingredients: Aluminum Zirconium Trichlorohydrex Gly (18%)

Purpose: Antiperspirant

INDICATIONS AND USAGE

Use: reduces underarm perspiration

WARNINGS

Warnings: For external use only. Do not use on broken skin. Stop us if rash or irritation occurs. Ask a doctor before use if you have kidney disease. Stop use and ask a doctor if rash or irritation occurs. If swallowed, get medical help or contact a Poison Control Center right away.

Keep out of reach of children.

DOSAGE AND ADMINISTRATION

Apply to underarms only.

QUESTIONS

Questions?: Call 022-67464241 or email us at zodhitacare@zodhita.com

INACTIVE INGREDIENT

Inactive Ingredients: Cyclopentasiloxane, Stearyl alcohol, Hydrogenated Castor Oil, Dipropylene Glycol Dibenzoate, Fragrance, PEG-8 Distearate, Silica, Aluminum Strach Octenyl Succinate, Mineral Oil, Cocos Nucifera (Coconut) Oil, Aloe Barbadensis (Aloe Vera) Leaf Extract

PACKAGE LABEL

Place holder text